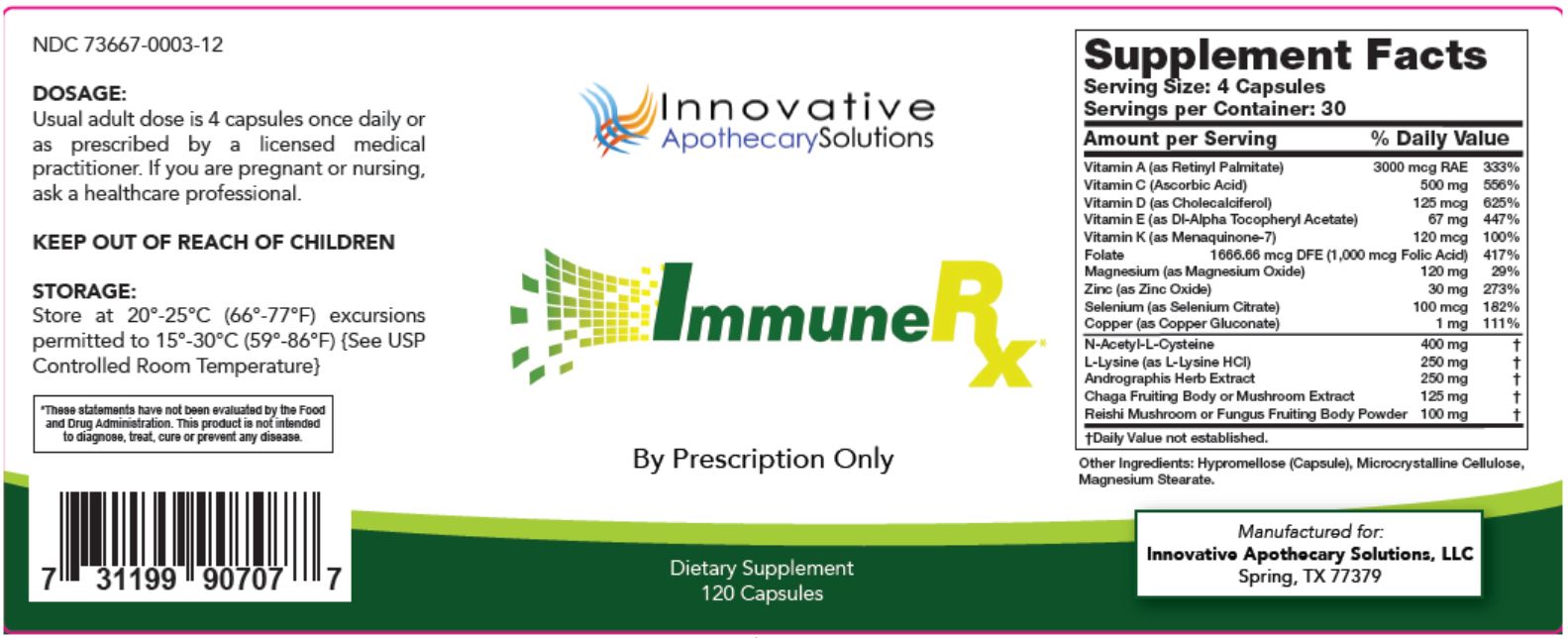 DRUG LABEL: ImmuneRx
NDC: 73667-003 | Form: CAPSULE
Manufacturer: Innovative Apothecary Solutions, LLC
Category: other | Type: DIETARY SUPPLEMENT
Date: 20201211

ACTIVE INGREDIENTS: VITAMIN A PALMITATE 3 mg/1 1; ASCORBIC ACID 500 mg/1 1; VITAMIN D 0.125 mg/1 1; .ALPHA.-TOCOPHEROL ACETATE 67 mg/1 1; MENAQUINONE 7 0.120 mg/1 1; FOLIC ACID 1 mg/1 1; MAGNESIUM OXIDE 120 mg/1 1; ZINC OXIDE 30 mg/1 1; COPPER GLUCONATE 1 mg/1 1; ACETYLCYSTEINE 400 mg/1 1; LYSINE HYDROCHLORIDE 250 mg/1 1; INONOTUS OBLIQUUS FRUITING BODY 125 mg/1 1; REISHI 100 mg/1 1; ANDROGRAPHIS PANICULATA WHOLE 250 mg/1 1
INACTIVE INGREDIENTS: MICROCRYSTALLINE CELLULOSE; MAGNESIUM STEARATE; SELENIUM

ImmuneRx

Dosage:

Usual adult dose is 4 capsules once daily or as prescribed by a licensed medical practitioner.

If pregnant

If you are pregnant or nursing, ask a healthcare provessional.

KEEP OUT OF REACH OF CHILDREN

Storage:

Store at 20°- 25°C (66°-77°F) excursions permitted to 15°- 30°C (59°-86°F) {See USP Controlled Room Temperature}

Indications and Usage

By Prescription Only

STATEMENT OF IDENTITY

ImmuneRx